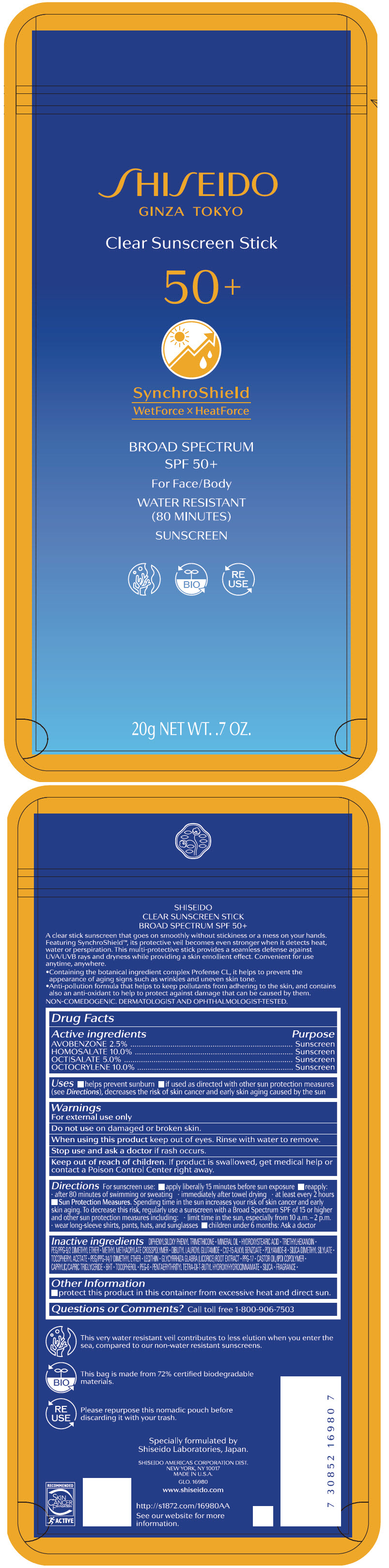 DRUG LABEL: SHISEIDO CLEAR SUNSCREEN SPF 50 Plus
NDC: 58411-616 | Form: STICK
Manufacturer: SHISEIDO AMERICAS CORPORATION
Category: otc | Type: HUMAN OTC DRUG LABEL
Date: 20241223

ACTIVE INGREDIENTS: AVOBENZONE 500 mg/20 g; HOMOSALATE 2000 mg/20 g; OCTISALATE 1000 mg/20 g; OCTOCRYLENE 2000 mg/20 g
INACTIVE INGREDIENTS: DIPHENYLSILOXY PHENYL TRIMETHICONE; MINERAL OIL; 12-HYDROXYSTEARIC ACID; TRIETHYLHEXANOIN; PEG/PPG-9/2 DIMETHYL ETHER; METHYL METHACRYLATE/GLYCOL DIMETHACRYLATE CROSSPOLYMER; ALKYL (C12-15) BENZOATE; DIBUTYL LAUROYL GLUTAMIDE; POLYAMIDE-8 (4500 MW); SILICA DIMETHYL SILYLATE; PPG-17; MEDIUM-CHAIN TRIGLYCERIDES; PEG/PPG-14/7 DIMETHYL ETHER; .ALPHA.-TOCOPHEROL ACETATE, DL-; POLYETHYLENE GLYCOL 300; PENTAERYTHRITOL TETRAKIS(3-(3,5-DI-TERT-BUTYL-4-HYDROXYPHENYL)PROPIONATE); BUTYLATED HYDROXYTOLUENE; SILICON DIOXIDE; GLYCYRRHIZA GLABRA; .ALPHA.-TOCOPHEROL

SHISEIDO CLEAR SUNSCREEN STICK SPF 50+

Drug Facts

ACTIVE INGREDIENT

Active ingredients | Purpose
AVOBENZONE 2.5% | Sunscreen
HOMOSALATE 10.0% | Sunscreen
OCTISALATE 5.0% | Sunscreen
OCTOCRYLENE 10.0% | Sunscreen

Uses

- helps prevent sunburn
- if used as directed with other sun protection measures (see Directions), decreases the risk of skin cancer and early skin aging caused by the sun

Warnings

For external use only

Do not use on damaged or broken skin

When using this product keep out of eyes. Rinse with water to remove.

Stop use and ask a doctor if rash occurs.

Keep out of reach of children. If product is swallowed, get medical help or contact a Poison Control Center right away.

Directions

For sunscreen use:

- apply liberally 15 minutes before sun exposure
- reapply:
  - after 80 minutes of swimming or sweating
  - immediately after towel drying
  - at least every two hours
- Sun Protection Measures. Spending time in the sun increases your risk of skin cancer and early skin aging. To decrease this risk, regularly use a sunscreen with a broad spectrum SPF of 15 or higher and other sun protection measures including:
  - limit time in the sun, especially from 10 a.m. – 2 p.m.
  - wear long-sleeve shirts, pants, hats, and sunglasses
  - children under 6 months: Ask a doctor

Inactive Ingredients

DIPHENYLSILOXY PHENYL TRIMETHICONE▪MINERAL OIL▪HYDROXYSTEARIC ACID▪TRIETHYLHEXANOIN▪PEG/PPG-9/2 DIMETHYL ETHER▪METHYL METHACRYLATE CROSSPOLYMER▪DIBUTYL LAUROYL GLUTAMIDE▪C12-15 ALKYL BENZOATE▪POLYAMIDE-8▪SILICA DIMETHYL SILYLATE▪TOCOPHERYL ACETATE▪PEG/PPG-14/7 DIMETHYL ETHER▪LECITHIN▪GLYCYRRHIZA GLABRA (LICORICE) ROOT EXTRACT▪PPG-17▪CASTOR OIL/IPDI COPOLYMER▪CAPRYLIC/CAPRIC TRIGLYCERIDE▪BHT▪TOCOPHEROL▪PEG-6▪PENTAERYTHRITYL TETRA-DI-T-BUTYL HYDROXYHYDROCINNAMATE▪SILICA▪FRAGRANCE▪

Other information

Protect this product in this container from excessive heat and direct sun.

Questions or comments?

Call toll free 1-800-906-7503

PRINCIPAL DISPLAY PANEL - 20 g Stick Pouch Label

SHISEIDO
GINZA TOKYO

Clear Sunscreen Stick
50+

SynchroShield
WetForce × HeatForce

BROAD SPECTRUM
SPF 50+
For Face/Body
WATER RESISTANT
(80 MINUTES)
SUNSCREEN

BIO

RE
USE

20g NET WT. .7 OZ.